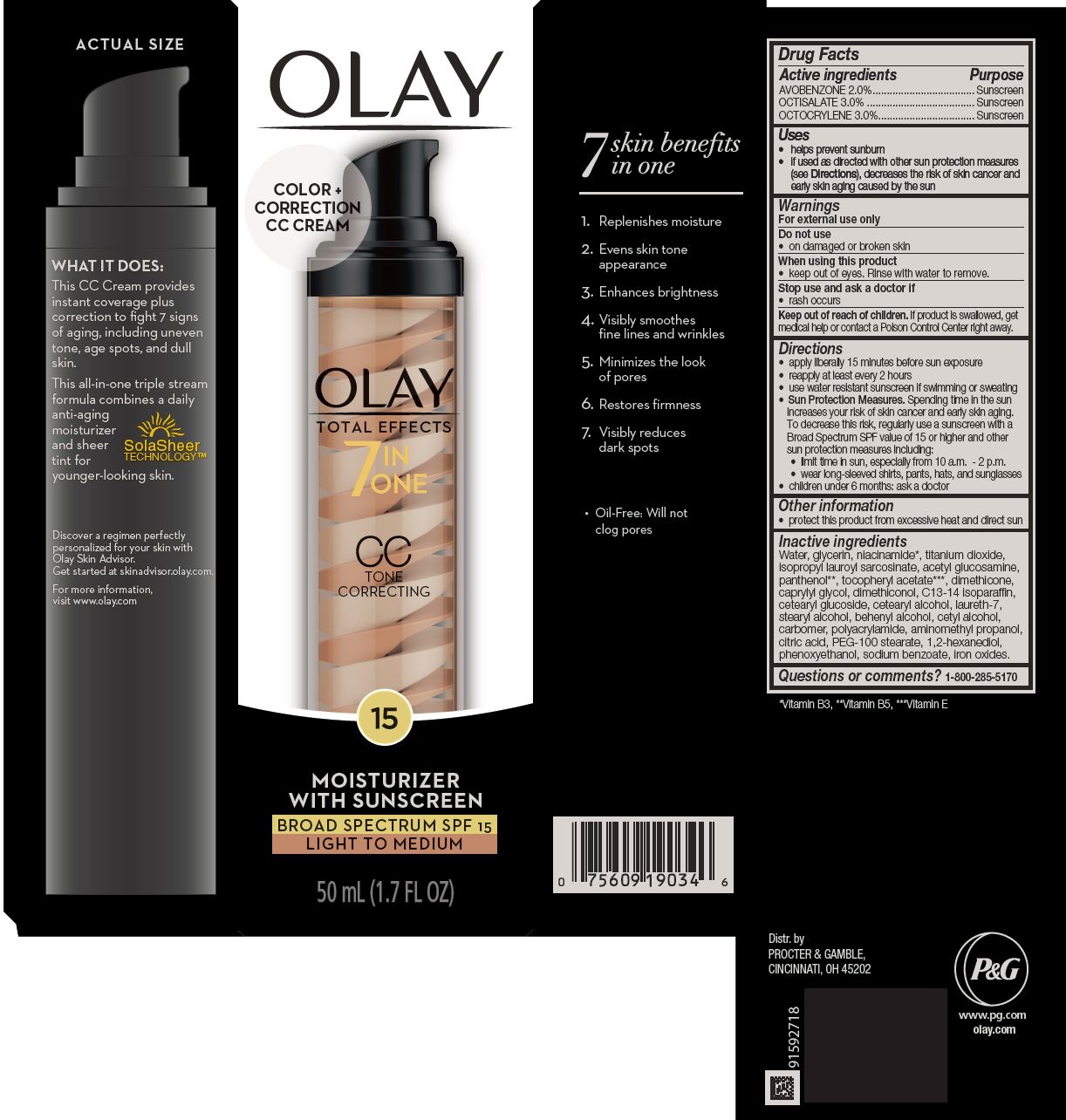 DRUG LABEL: Olay Total Effects CC Tone Correcting
NDC: 37000-355 | Form: CREAM
Manufacturer: The Procter & Gamble Manufacturing Company
Category: otc | Type: HUMAN OTC DRUG LABEL
Date: 20251218

ACTIVE INGREDIENTS: AVOBENZONE 2 g/1 mL; OCTISALATE 3 g/1 mL; OCTOCRYLENE 3 g/1 mL
INACTIVE INGREDIENTS: GLYCERIN; WATER; NIACINAMIDE; TITANIUM DIOXIDE; N-ACETYLGLUCOSAMINE; .ALPHA.-TOCOPHEROL ACETATE; PANTHENOL; DIMETHICONE; CAPRYLYL GLYCOL; DOCOSANOL; STEARYL ALCOHOL; CETYL ALCOHOL; LAURETH-7; AMINOMETHYL PROPANEDIOL; CITRIC ACID MONOHYDRATE; PEG-100 STEARATE; CETEARYL GLUCOSIDE; CETOSTEARYL ALCOHOL; C13-14 ISOPARAFFIN; 1,2-HEXANEDIOL; PHENOXYETHANOL; FERRIC OXIDE RED; ISOPROPYL LAUROYL SARCOSINATE; POLYACRYLAMIDE (1300000 MW); SODIUM BENZOATE; CARBOXYPOLYMETHYLENE; DIMETHICONOL (100000 CST)

Olay Total Effects CC Tone Correcting
Broad Spectrum SPF 15 Light to Medium

Drug Facts

ACTIVE INGREDIENT

Active ingredients | Purpose
Avobenzone 2% | Sunscreen
Octisalate 3% | Sunscreen
Octocrylene 3% | Sunscreen

Uses

- helps prevent sunburn
- if used as directed with other sun protection measures (see Directions), decreases the risk of skin cancer and early skin aging caused by the sun

Warnings

For external use only

Do not use

- on damaged or broken skin

When using this product

- keep out of eyes. Rinse with water to remove.

Stop use and ask a doctor if

- rash occurs

Keep out of reach of children. If product is swallowed, get medical help or contact a Poison Control Center right away.

Directions

- apply liberally 15 minutes before sun exposure
- reapply at least every 2 hours
- use water resistant sunscreen if swimming or sweating
- Sun Protection Measures. Spending time in the sun increases your risk of skin cancer and early skin aging. To decrease this risk, regularly use a sunscreen with a Broad Spectrum SPF value of 15 or higher and other sun protection measures including:
  - limit time in sun, especially from 10 a.m. - 2 p.m.
  - wear long-sleeved shirts, pants, hats, and sunglasses
- children under 6 months: ask a doctor

Other information

- protect this product from excessive heat and direct sun

Inactive ingredients

Water, glycerin, niacinamide*, titanium dioxide, isopropyl lauroyl sarcosinate, acetyl glucosamine, panthenol**, tocopheryl acetate***, dimethicone, caprylyl glycol, dimethiconol, C13-14 isoparaffin, cetearyl glucoside, cetearyl alcohol, laureth-7, stearyl alcohol, behenyl alcohol, cetyl alcohol, carbomer, polyacrylamide, aminomethyl propanol, citric acid, PEG-100 stearate, 1,2-hexanediol, phenoxyethanol, sodium benzoate, iron oxides.

*Vitamin B3, **Vitamin B5, ***Vitamin E

Questions or comments?

Call 1-800-285-5170

Distr. by
PROCTER & GAMBLE,
CINCINNATI, OH 45202

PRINCIPAL DISPLAY PANEL - 50 mL Bottle Carton

COLOR +
CORRECTION

CC CREAM

OLAY®
Total Effects®

7
IN
ONE

CC

TONE CORRECTING
15

MOISTURIZER with sunscreen

BROAD SPECTRUM SPF 15
light to medium

50 mL (1.7 FL OZ)